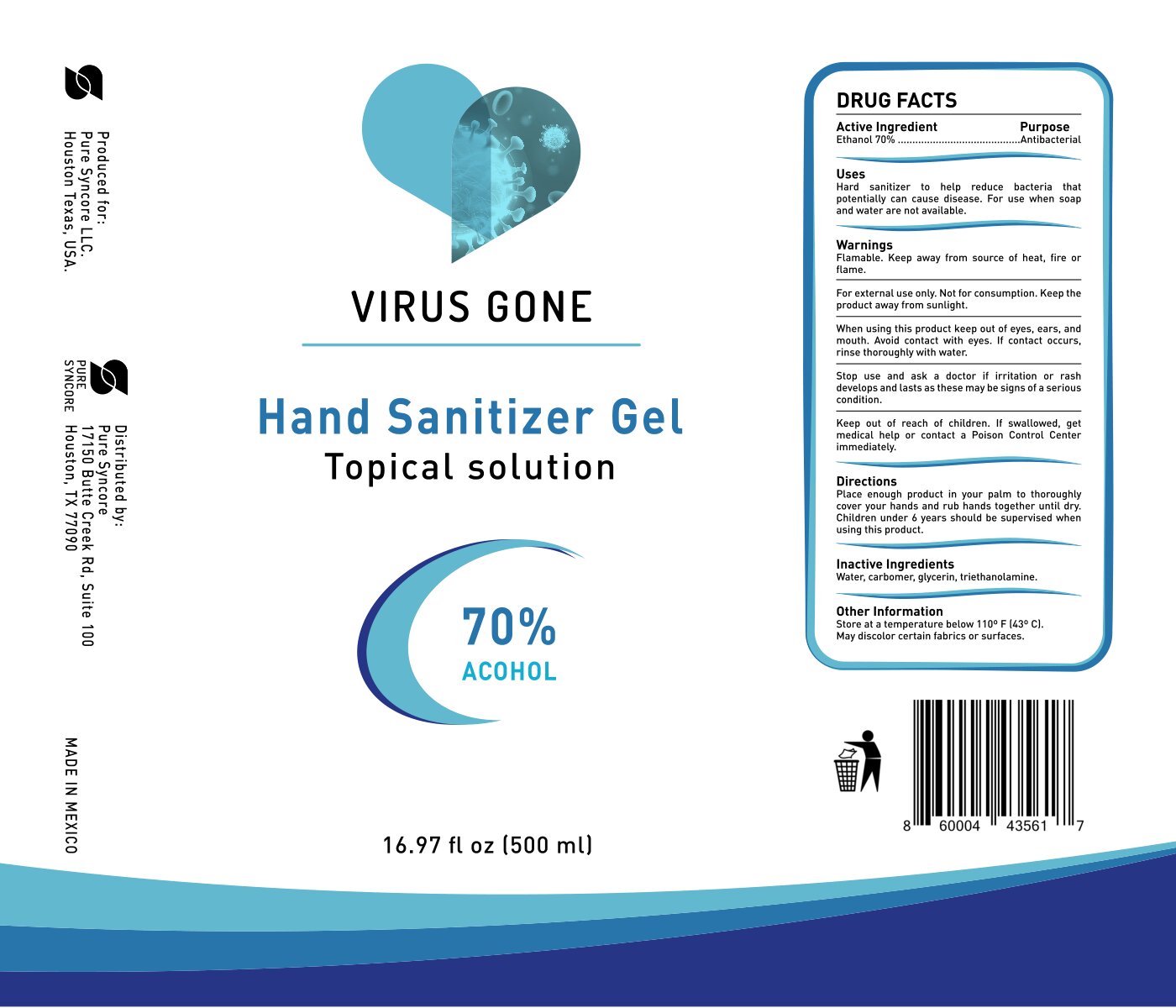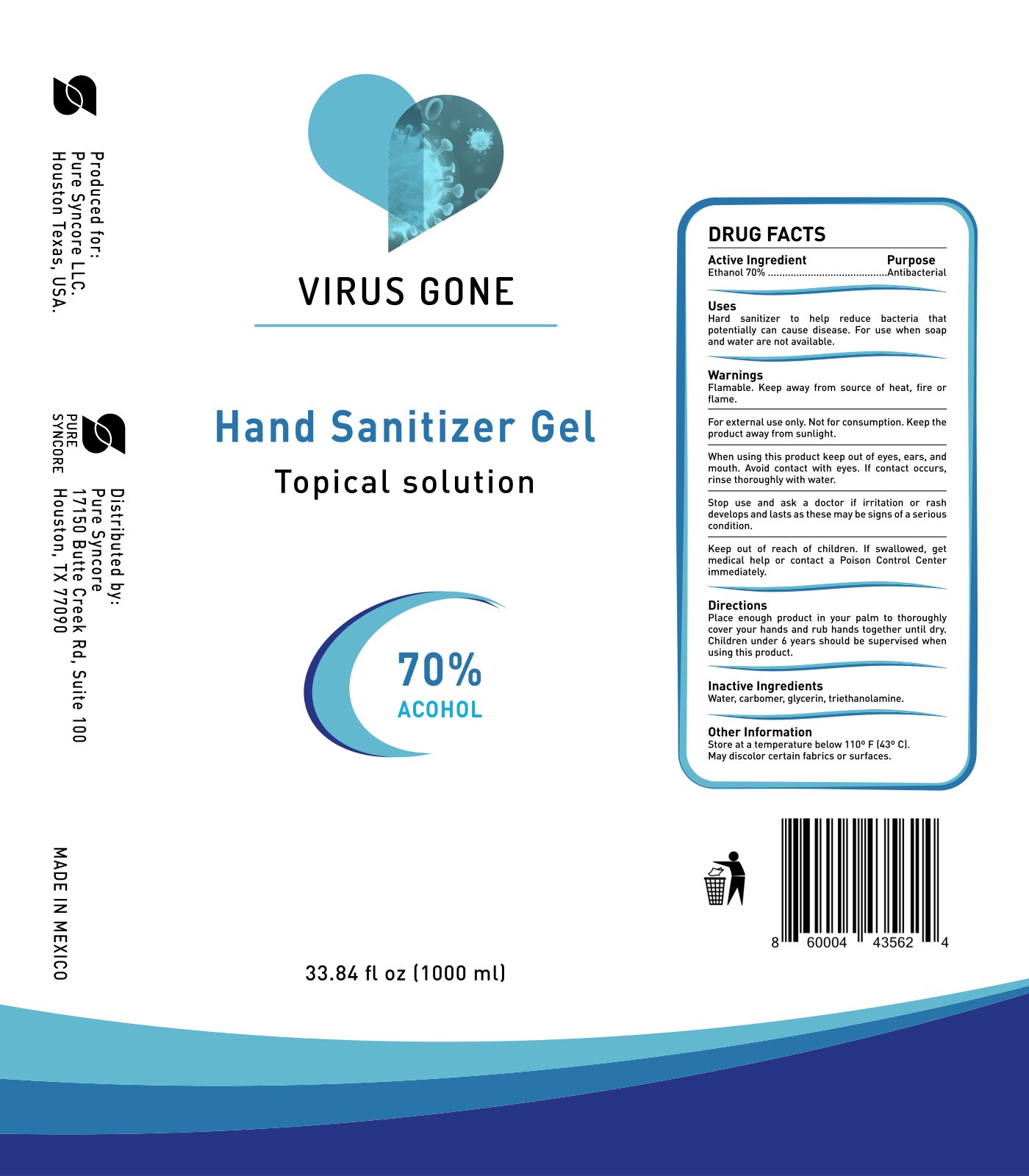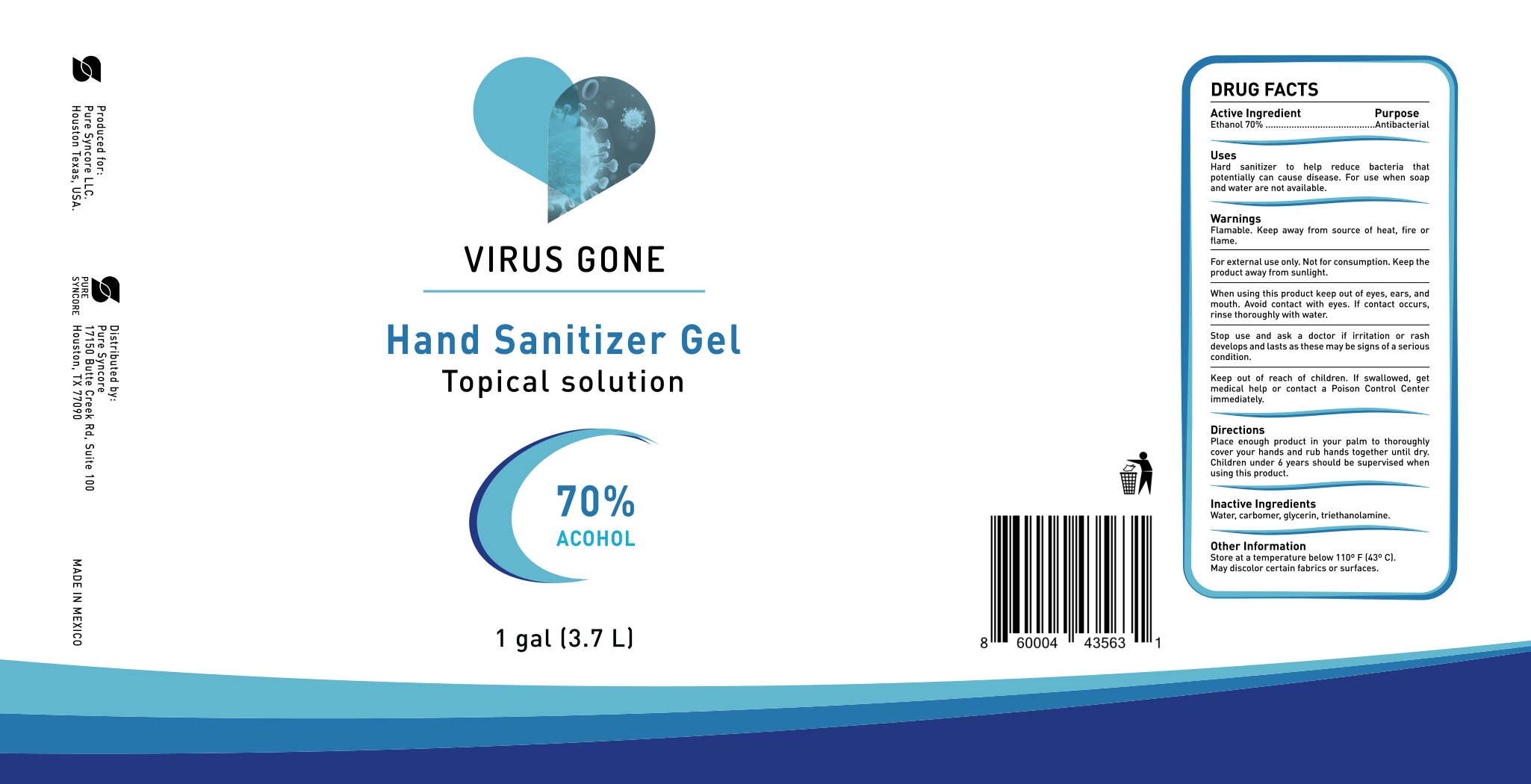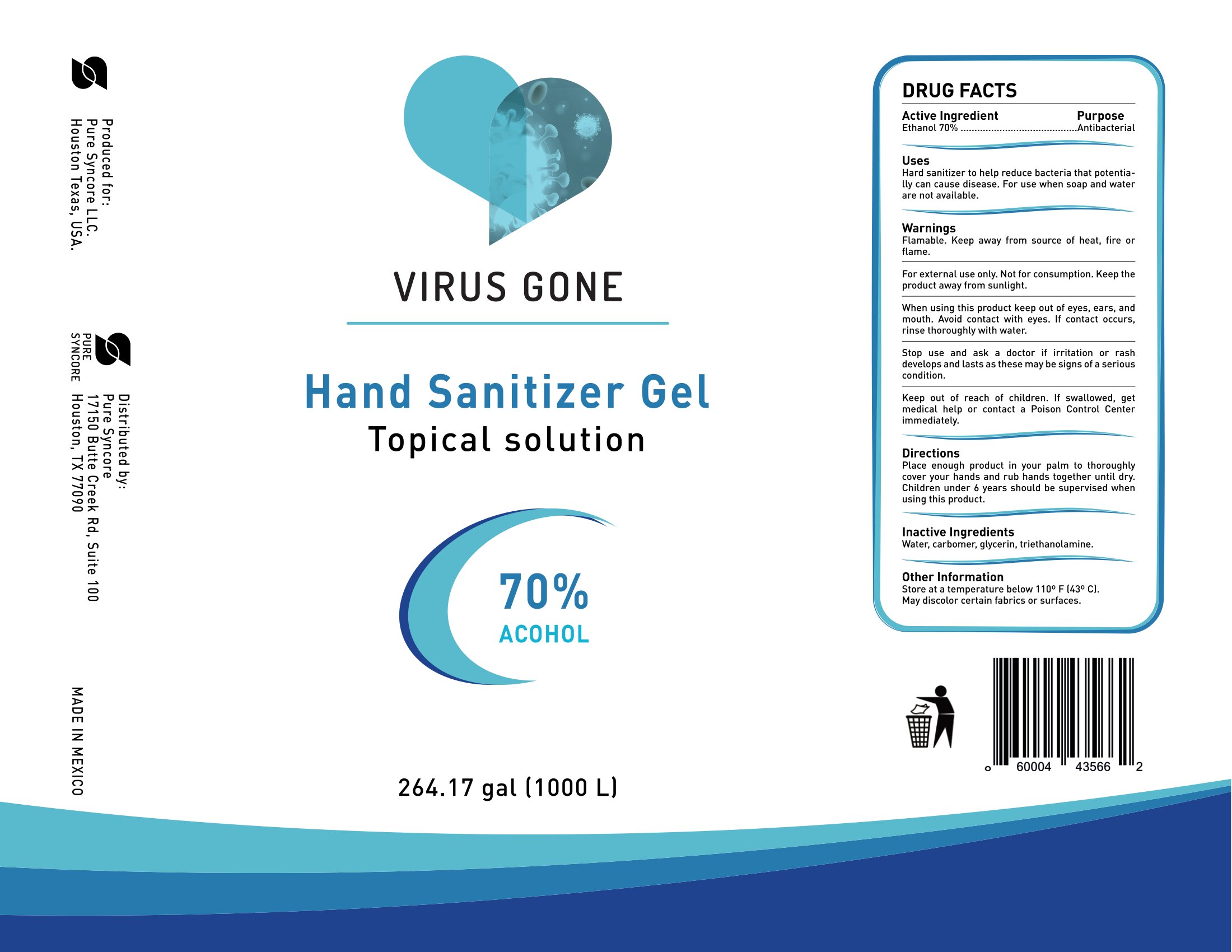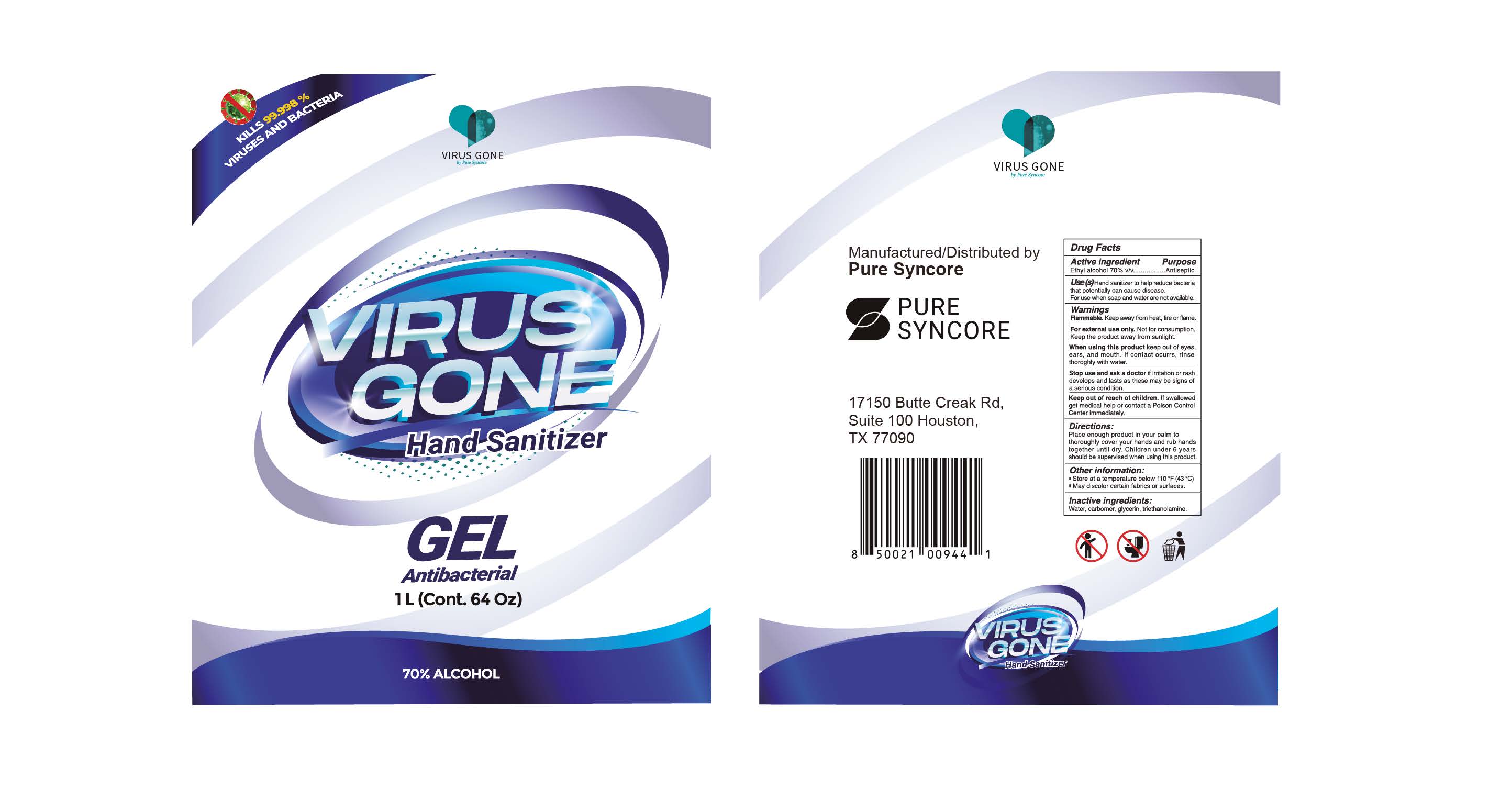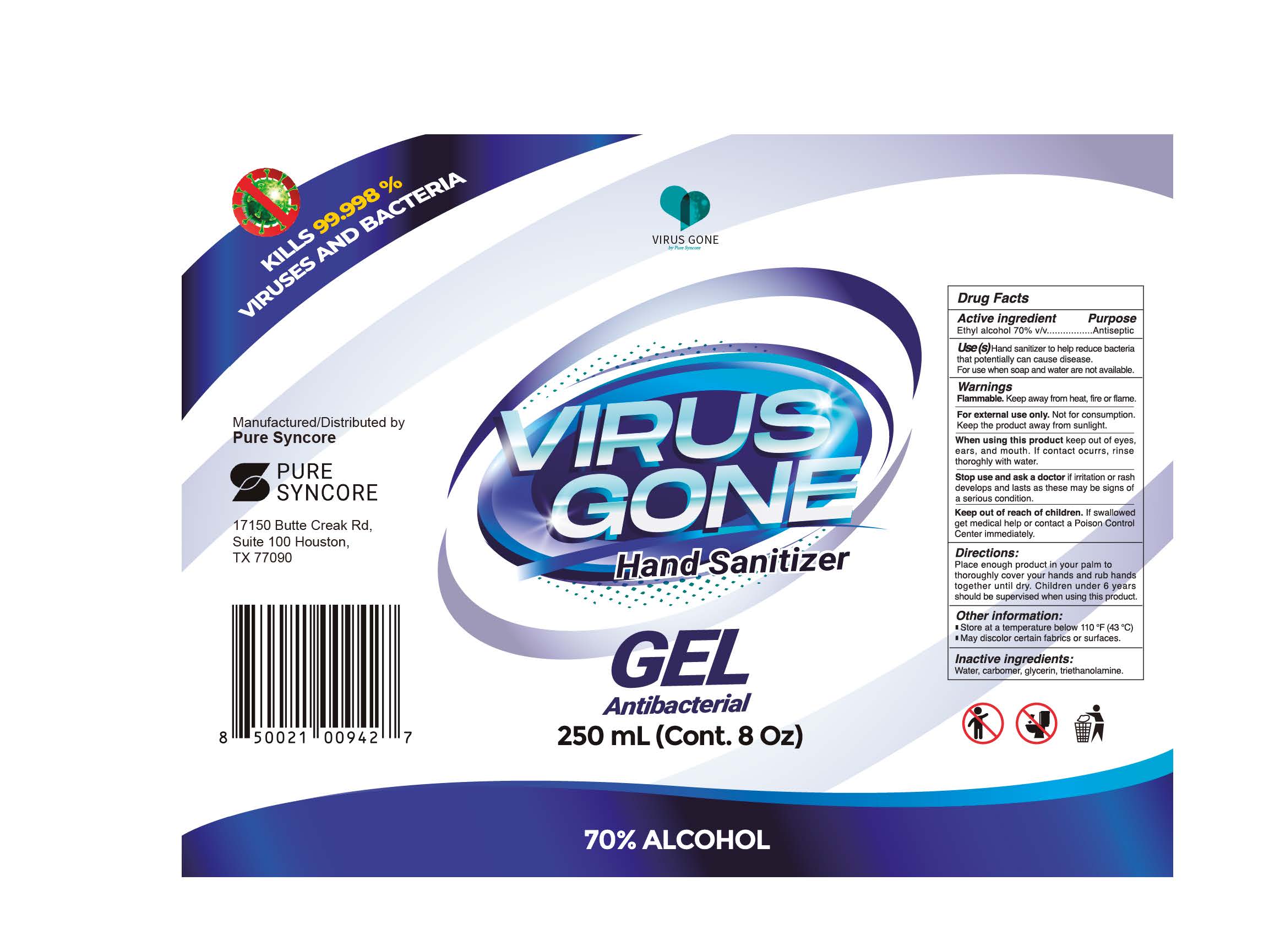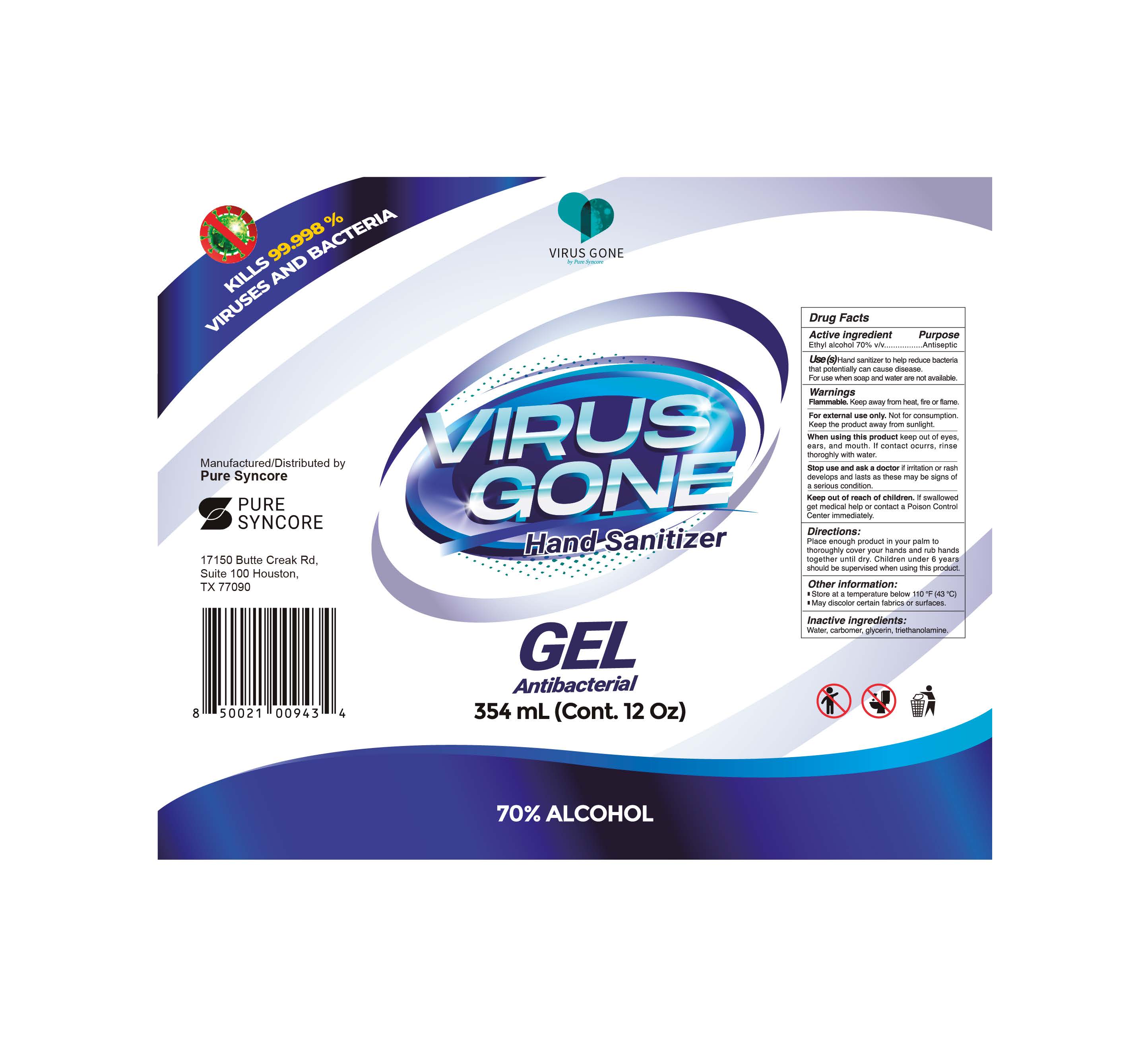 DRUG LABEL: Virus Gone
NDC: 78785-001 | Form: GEL
Manufacturer: Pure Syncore LLC
Category: otc | Type: HUMAN OTC DRUG LABEL
Date: 20210111

ACTIVE INGREDIENTS: ALCOHOL 69.4 mL/100 mL
INACTIVE INGREDIENTS: TROLAMINE 0.25 mL/100 mL; CARBOMER HOMOPOLYMER, UNSPECIFIED TYPE 0.4 mL/100 mL; GLYCERIN 0.3 mL/100 mL; WATER 29.65 mL/100 mL

78785-001 Virus Gone - Alcohol 70%

Active Ingredient(s)

Alcohol 70% v/v. Purpose: Antiseptic

Purpose

Antiseptic, Hand Sanitizer

Use

Hand Sanitizer to help reduce bacteria that potentially can cause disease. For use when soap and water are not available.

Warnings

For external use only. Flammable. Keep away from heat or flame

Do not use

- in children less than 2 months of age
- on open skin wounds

When using this product keep out of eyes, ears, and mouth. In case of contact with eyes, rinse eyes thoroughly with water.
Stop use and ask a doctor if irritation or rash occurs. These may be signs of a serious condition.
Keep out of reach of children. If swallowed, get medical help or contact a Poison Control Center right away.

Stop use and ask a doctor if irritation or rash occurs. These may be signs of a serious condition.

Keep out of reach of children. If swallowed, get medical help or contact a Poison Control Center right away.

Directions

- Place enough product on hands to cover all surfaces. Rub hands together until dry.
- Supervise children under 6 years of age when using this product to avoid swallowing.

Other information

- Store between 15-30C (59-86F)
- Avoid freezing and excessive heat above 40C (104F)

Inactive ingredients

water, carbomer, glycerin, triethanolamine

Package Label - Principal Display Panel

500 mL NDC: 78785-001-01

1000 mL NDC: 78785-001-02

3785 mL NDC: 78785-001-03

1000000 mL NDC: 78785-001-04

236mL NDC: 78785-001-09

354mL NDC: 78785-001-10

1892mL NDC: 78785-001-11